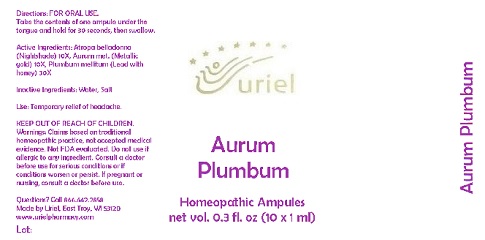 DRUG LABEL: Aurum Plumbum
NDC: 48951-1200 | Form: LIQUID
Manufacturer: Uriel Pharmacy Inc.
Category: homeopathic | Type: HUMAN OTC DRUG LABEL
Date: 20180423

ACTIVE INGREDIENTS: ATROPA BELLADONNA 10 [hp_X]/1 mL; GOLD 10 [hp_X]/1 mL; LEAD 30 [hp_X]/1 mL; HONEY 30 [hp_X]/1 mL
INACTIVE INGREDIENTS: WATER; SODIUM CHLORIDE

Aurum Plumbum

INDICATIONS AND USAGE

Directions: FOR ORAL USE.

DOSAGE AND ADMINISTRATION

Take the contents of one ampule under the tongue and hold for 30 seconds, then swallow.

ACTIVE INGREDIENT

Active Ingredients: Atropa belladonna (Nightshade) 10X, Aurum met. (Metallic gold) 10X, Plumbum mellitum (Lead with honey) 30X

Inactive Ingredients: Water, Salt

PURPOSE

Use: Temporary relief of headache.

KEEP OUT OF REACH OF CHILDREN.

WARNINGS

Warnings: Claims based on traditional homeopathic practice, not accepted medical evidence. Not FDA evaluated. Do not use if allergic to any ingredient. Consult a doctor before use for serious conditions or if conditions worsen or persist. If pregnant or nursing, consult a doctor before use.

QUESTIONS

Questions? Call 866.642.2858 Made by Uriel, East Troy, WI 53120 www.urielpharmacy.com